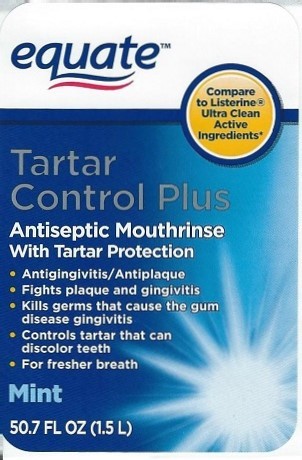 DRUG LABEL: Equate Tartar Control Plus
NDC: 49035-536 | Form: LIQUID
Manufacturer: Wal-Mart Stores, Inc.
Category: otc | Type: HUMAN OTC DRUG LABEL
Date: 20230106

ACTIVE INGREDIENTS: EUCALYPTOL 0.092 g/1 mL; MENTHOL 0.042 g/1 mL; METHYL SALICYLATE 0.06 g/1 mL; THYMOL 0.064 g/1 mL
INACTIVE INGREDIENTS: WATER; ALCOHOL; SORBITOL; POLOXAMER 407; BENZOIC ACID; ZINC CHLORIDE; SODIUM BENZOATE; SUCRALOSE; SACCHARIN SODIUM; FD&C BLUE NO. 1

Equate Tartar Control Plus

Drug Facts

Active ingredients

Eucalyptol 0.092%, Menthol 0.042%

Methyl Salicylate 0.060%, Thymol 0.064%

Purpose

Antigingivitis, Antiplaque

Antigingivitis, Antiplaque

INDICATIONS AND USAGE

Use Kills germs that cause gingivitis, plaque, and bad breath. Contains zinc chloride to prevent tartar build-up that stains teeth.

Warnings

Do not use If you have painful or swollen gums, pus from the gum line, loose teeth or increased spacing between the teeth. See your dentist immediately. These may be signs of periodontitis, a serious form of gum disease.

Stop use and ask a dentist if gingivitis, bleeding or redness persists for more than 2 weeks.

Keep out of reach of children. If more than used for rinsing is accidentally swallowed, get medical help or contact a Poison Control Center right away.

Directions

adults and children 12 years of age and older | vigorously swish 20 mL (2/3 FL OZ or 4 teaspoonfuls); between teeth for 30 seconds then spit out; do not swallow
children under 12 years of age | consult a dentist or doctor

- this rinse is not intended to replace brushing or flossing.

Other information Cold weather may cloud this product. Its antiseptic properties are not affected. Store at room temperature(59°-86°F).

INACTIVE INGREDIENT

Inactive ingredients Water, Alcohol (21.6%), Sorbitol, Flavoring, Poloxamer 407, Benzoic Acid, Zinc Chloride, Sodium Benzoate, Sucralose, Sodium Saccharin, FD&C Blue 1.

PACKAGE LABEL

equate™

Tarter Control Plus

Antiseptic Mouthrinse with Tartar Protection

- Antigingivitis/Antiplaque
- Fights plaque and gingivitis
- Kills germs that cause the gum disease gingivitis
- Controls tartar that can discolor teeth
- For fresher breath

Mint

50.7 FL OZ (1.5 L)